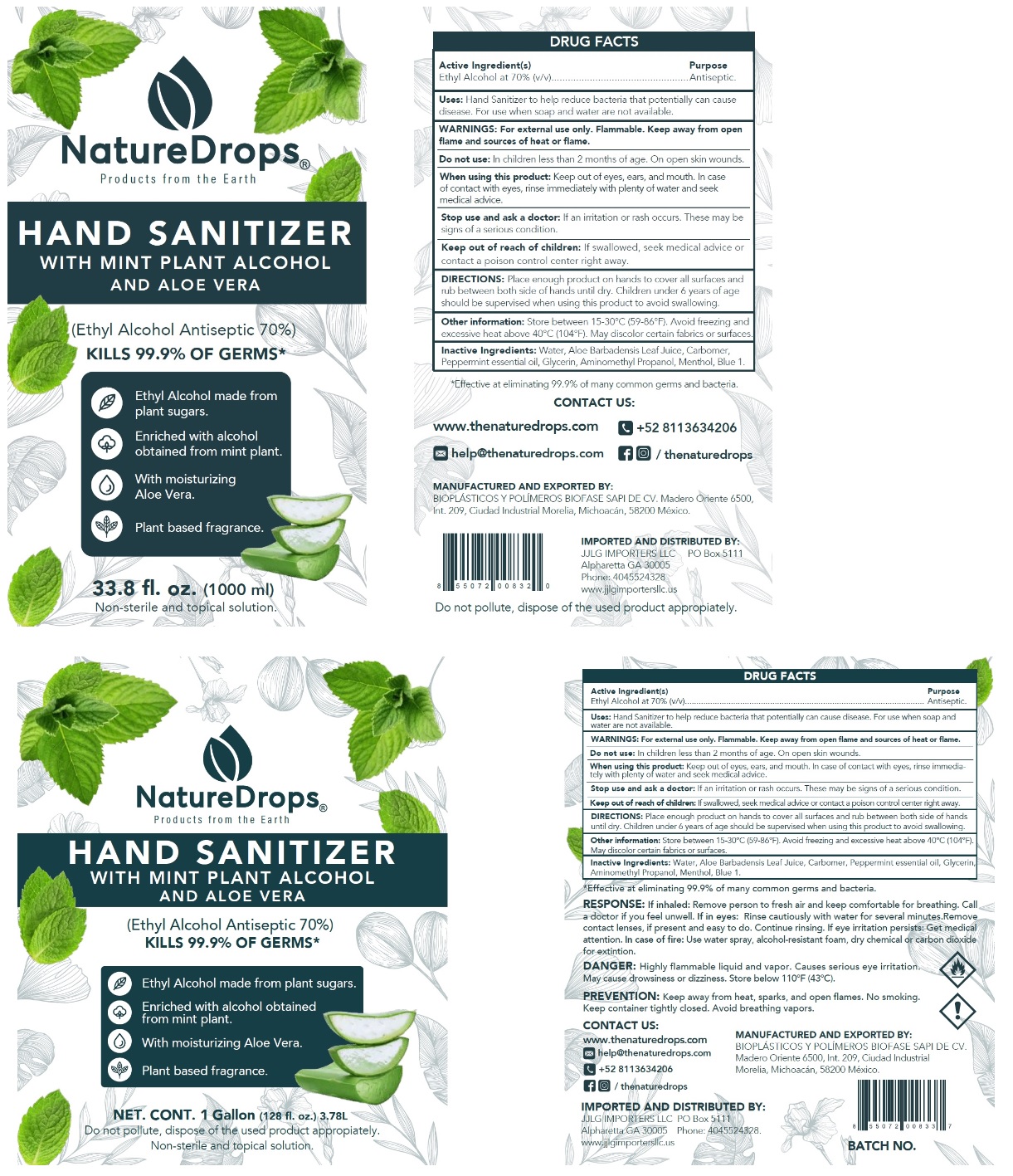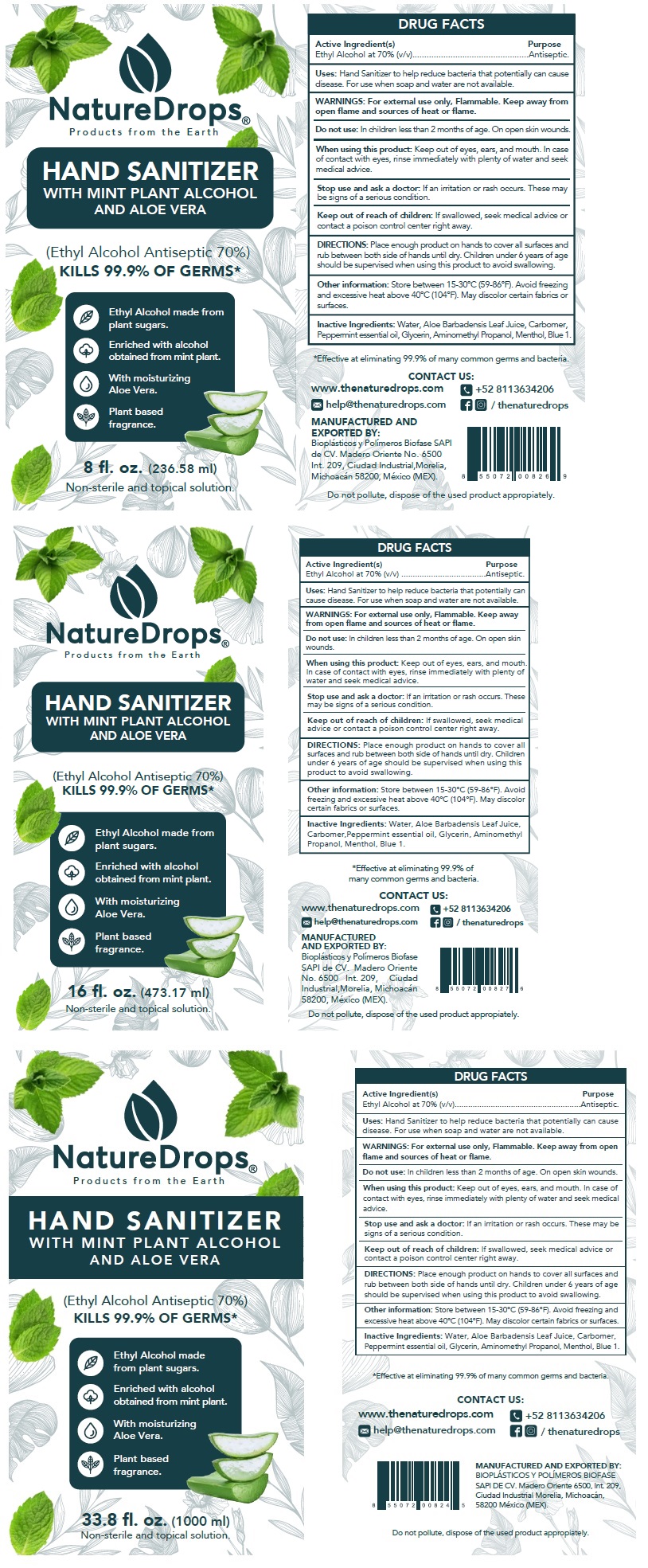 DRUG LABEL: NatureDrops Hand Sanitizer
NDC: 77452-003 | Form: GEL
Manufacturer: Bioplasticos y Polimeros BIOFASE, S.A.P.I. de C.V.
Category: otc | Type: HUMAN OTC DRUG LABEL
Date: 20200701

ACTIVE INGREDIENTS: ALCOHOL 0.7 mL/1 mL
INACTIVE INGREDIENTS: WATER; ALOE VERA LEAF; CARBOMER HOMOPOLYMER, UNSPECIFIED TYPE; GLYCERIN; AMINOMETHYLPROPANOL; MENTHOL, UNSPECIFIED FORM; FD&C BLUE NO. 1

NatureDrops Hand Sanitizer

Active Ingredient(s)

Ethyl Alcohol at 70% (v/v)

Purpose

Antiseptic.

Uses:

Hand Sanitizer to help reduce bacteria that potentially can cause disease. For use when soap and water are not available.

WARNINGS:

For external use only. Flammable. Keep away from open flame and sources of heat or flame.

Do not use: In children less than 2 months of age. On open skin wounds.

When using this product: Keep out of eyes, ears, and mouth. In case of contact with eyes, rinse immediately with plenty of water and seek medical advice.

Stop use and ask a doctor: If an irritation or rash occurs. These may be signs of a serious condition.

Keep out of reach of children: If swallowed, seek medical advice or contact a poison control center right away.

DIRECTIONS:

Place enough product on hands to cover all surfaces and rub between both side of hands until dry. Children under 6 years of age should be supervised when using this product to avoid swallowing.

Other information:

Store between 15-30°C (59-86°F). Avoid freezing and excessive heat above 40°C (104°F). May discolor certain fabrics or surfaces.

Inactive Ingredients:

Water, Aloe Barbadensis Leaf Juice, Carbomer, Peppermint essential oil, Glycerin, Aminomethyl Propanol, Menthol, Blue 1.